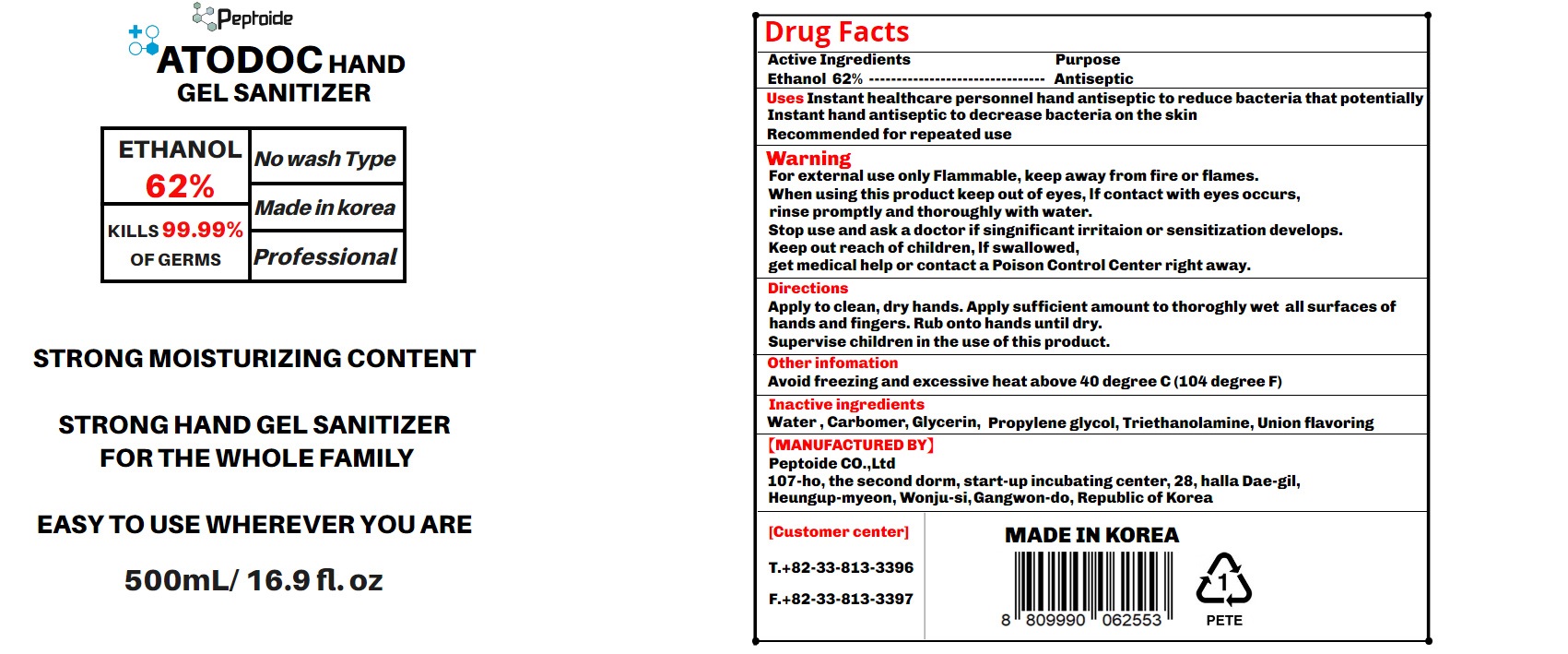 DRUG LABEL: ATODOC HAND gel SANITIZER
NDC: 77654-0001 | Form: GEL
Manufacturer: Peptoide Co.,Ltd
Category: otc | Type: HUMAN OTC DRUG LABEL
Date: 20200517

ACTIVE INGREDIENTS: ALCOHOL 62 mL/100 mL
INACTIVE INGREDIENTS: GLYCERIN; PROPYLENE GLYCOL; ALOE VERA LEAF; CARBOMER 940; TROLAMINE; WATER

Drug Facts

ACTIVE INGREDIENT

alcohol

INACTIVE INGREDIENT

Water

Carbomer

Triethanolamine

Propylene glycol

Glycerine

Fragrance(union flavoring)

PURPOSE

Sterilization of hands and skin

KEEP OUT OF REACH OF THE CHILDREN

INDICATIONS AND USAGE

Apply to clean, dry hands. Apply sufficient amount to thoroughly wet all surfaces of hands and fingers. Rub onto hands until dry.

Supervise children in the use of this product.

WARNINGS

■ Flammable. Keep away from fire or flame.

■ For external use only.

■ Do not use in eyes.

■ lf swallowed, get medical help promptly.

■ Stop use, ask doctor lf irritation occurs.

■ Keep out of reach of children.

DOSAGE AND ADMINISTRATION

for external use only